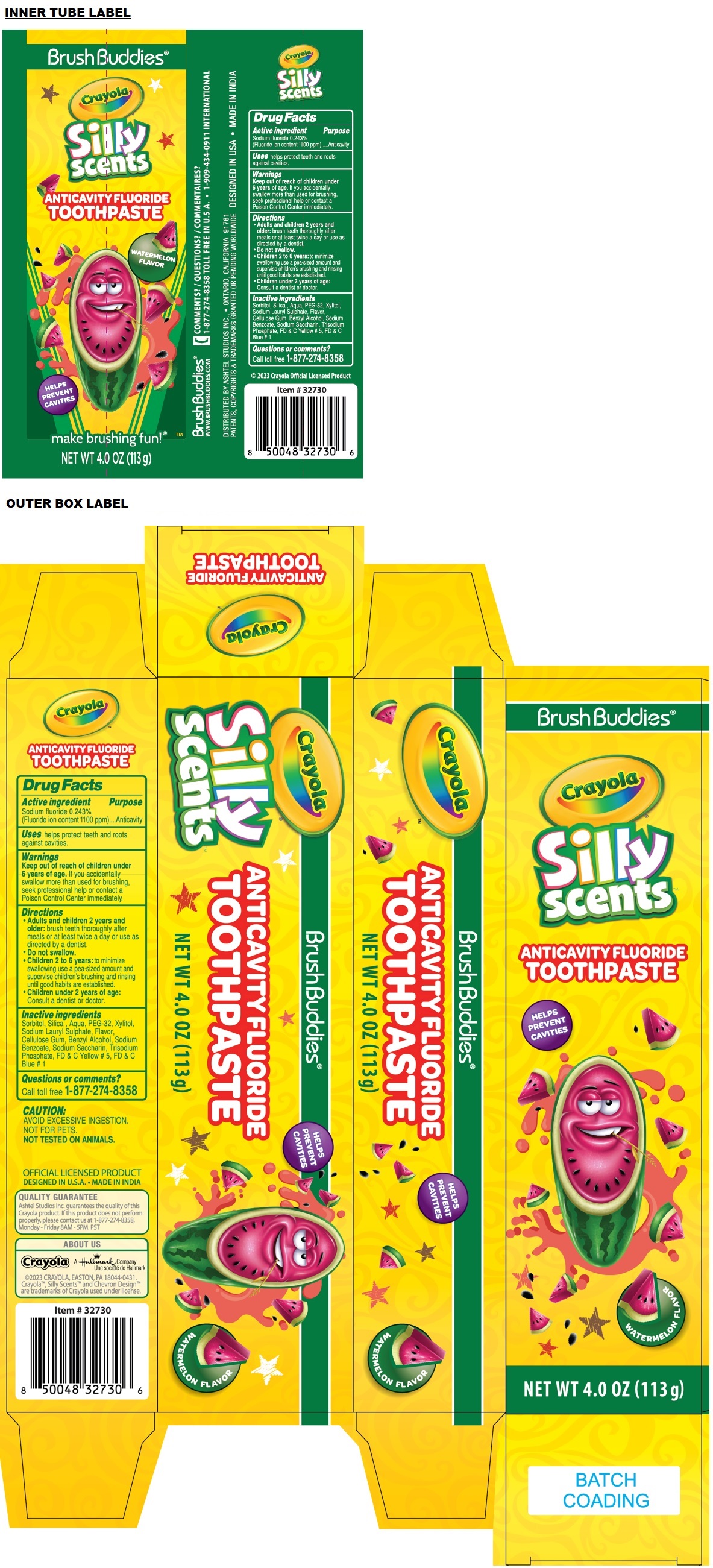 DRUG LABEL: Crayola ANTICAVITY WATERMELON FLAVOR
NDC: 70108-081 | Form: PASTE, DENTIFRICE
Manufacturer: Ashtel Studios, Inc.
Category: otc | Type: HUMAN OTC DRUG LABEL
Date: 20250319

ACTIVE INGREDIENTS: SODIUM FLUORIDE 0.243 g/100 g
INACTIVE INGREDIENTS: SORBITOL; SILICON DIOXIDE; WATER; POLYETHYLENE GLYCOL 1600; XYLITOL; SODIUM LAURYL SULFATE; CARBOXYMETHYLCELLULOSE SODIUM, UNSPECIFIED; BENZYL ALCOHOL; SODIUM BENZOATE; SACCHARIN SODIUM; SODIUM PHOSPHATE, TRIBASIC, ANHYDROUS; FD&C YELLOW NO. 5; FD&C BLUE NO. 1

Crayola ANTICAVITY FLUORIDE TOOTHPASTE - WATERMELON FLAVOR

Active ingredient

Sodium fluoride 0.243%
(Fluoride ion content 1100 ppm)

Purpose

Anticavity

Uses

helps protect teeth and roots against cavities.

Warnings

Keep out of reach of children under 6 years of age. If you accidentally swallow more than used for brushing, seek professional help or contact a Poison Control Center immediately.

Directions

• Adults and children 2 years and older: brush teeth thoroughly after meals or at least twice a day or use as directed by a dentist.
• Do not swallow.
• Children 2 to 6 years: to minimize swallowing use a pea-sized amount and supervise children's brushing and rinsing until good habits are established.
• Children under 2 years of age: Consult a dentist or doctor.

Inactive ingredients

Sorbitol, Silica, Aqua, PEG -32, Xylitol, Sodium Lauryl Sulphate, Flavor, Cellulose Gum, Benzyl Alcohol, Sodium Benzoate, Sodium Saccharin, Trisodium Phosphate, FD & C Yellow # 5, FD & C Blue # 1

Questions or comments?

Call toll free 1-877-274-8358

BrushBuddies®

Silly scents

HELPS PREVENT CAVITIES

WATERMELON FLAVOR

CAUTION:
AVOID EXCESSIVE INGESTION.
NOT FOR PETS.
NOT TESTED ON ANIMALS.

OFFICIAL LICENSED PRODUCT

DESIGNED IN U.S.A. • MADE IN INDIA

QUALITY GUARANTEE

Ashtel Studios Inc. guarantees the quality of this Crayola product. If this product does not perform properly, please contact us at 1-877-274-8358, Monday-Friday 8AM-5PM. PST

ABOUT US

Crayola A Hallmark Company

©2023 CRAYOLA, EASTON, PA 18044-0431.

CrayolaTM, Silly ScentsTM and Chevron DesignTM are trademarks of Crayola used under license.

make brushing fun!®

WWW.BRUSHBUDDIES.COM

• 1-909-434-0911 INTERNATIONAL

DISTRIBUTED BY ASHTEL STUDIOS INC., • ONTARIO, CALIFORNIA 91761

PATENTS, COPYRIGHTS & TRADEMARKS GRANTED OR PENDING WORLDWIDE